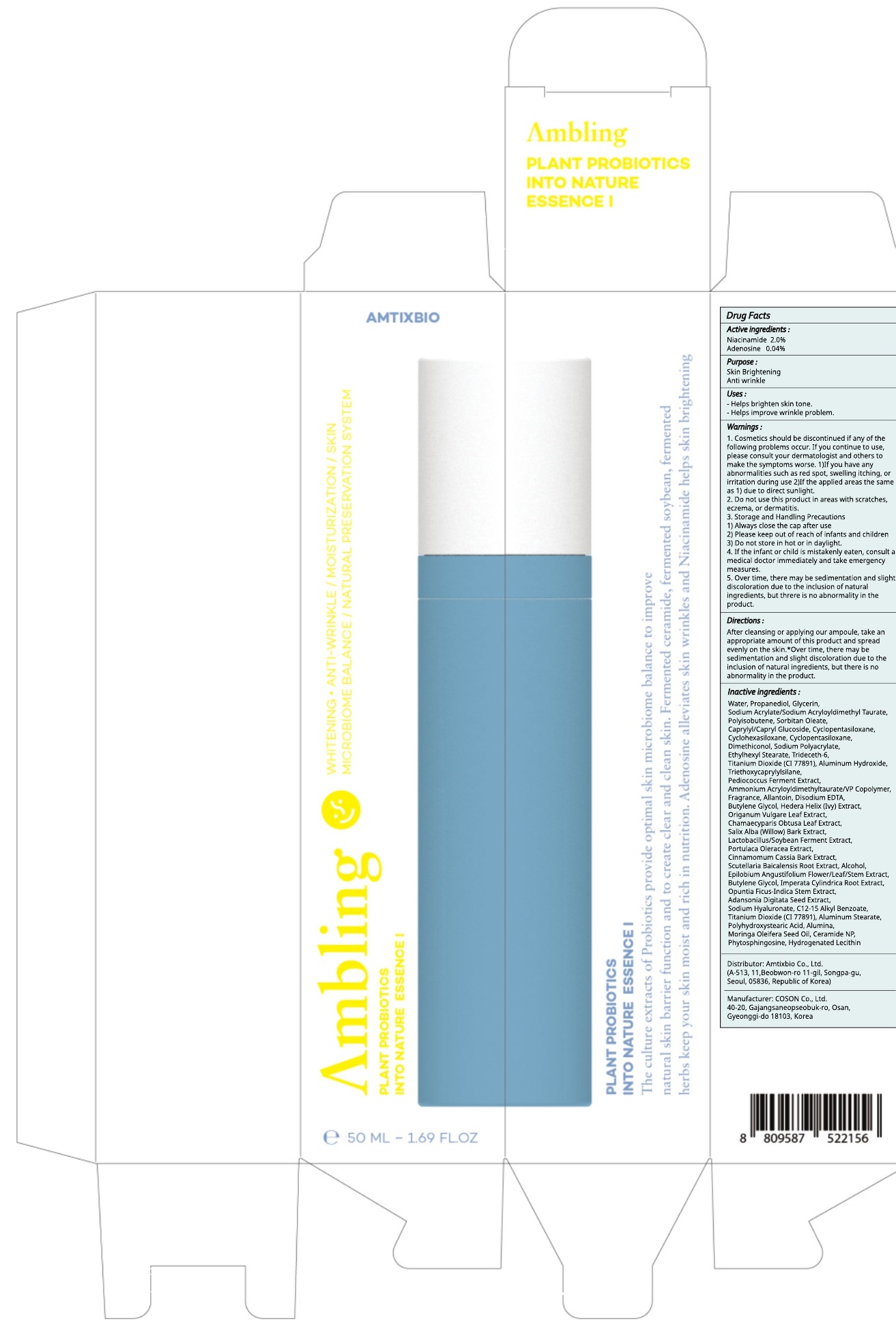 DRUG LABEL: Ambling Plant Probiotics Into Nature Essence I
NDC: 73456-030 | Form: LIQUID
Manufacturer: Amtixbio Co., Ltd.
Category: otc | Type: HUMAN OTC DRUG LABEL
Date: 20191202

ACTIVE INGREDIENTS: Niacinamide 1.00 g/50 mL; Adenosine 0.02 g/50 mL
INACTIVE INGREDIENTS: Water; Propanediol

ACTIVE INGREDIENT

Active ingredients: Niacinamide 2.0%, Adenosine 0.04%

INACTIVE INGREDIENT

Inactive ingredients:

Water, Propanediol, Glycerin, Sodium Acrylate/Sodium Acryloyldimethyl Taurate, Polyisobutene, Sorbitan Oleate, Caprylyl/Capryl Glucoside, Cyclopentasiloxane, Cyclohexasiloxane, Cyclopentasiloxane, Dimethiconol, Sodium Polyacrylate, Ethylhexyl Stearate, Trideceth-6, Titanium Dioxide (CI 77891), Aluminum Hydroxide, Triethoxycaprylylsilane, Pediococcus Ferment Extract, Ammonium Acryloyldimethyltaurate/VP Copolymer, Fragrance, Allantoin, Disodium EDTA, Butylene Glycol, Hedera Helix (Ivy) Extract, Origanum Vulgare Leaf Extract, Chamaecyparis Obtusa Leaf Extract, Salix Alba (Willow) Bark Extract, Lactobacillus/Soybean Ferment Extract, Portulaca Oleracea Extract, Cinnamomum Cassia Bark Extract, Scutellaria Baicalensis Root Extract, Alcohol, Epilobium Angustifolium Flower/Leaf/Stem Extract, Butylene Glycol, Imperata Cylindrica Root Extract, Opuntia Ficus-Indica Stem Extract, Adansonia Digitata Seed Extract, Sodium Hyaluronate, C12-15 Alkyl Benzoate, Titanium Dioxide (CI 77891), Aluminum Stearate, Polyhydroxystearic Acid, Alumina, Moringa Oleifera Seed Oil, Ceramide NP, Phytosphingosine, Hydrogenated Lecithin

PURPOSE

Purpose: Skin Brightening, Anti wrinkle

WARNINGS

1. Cosmetics should be discontinued if any of the following problems occur. If you continue to use, please consult your dermatologist and others to make the symptoms worse. 1)If you have any abnormalities such as red spot, swelling itching, or irritation during use 2)If the applied areas the same as 1) due to direct sunlight.
2. Do not use this product in areas with scratches, eczema, or dermatitis.
3. Storage and Handling Precautions
1) Always close the cap after use
2) Please keep out of reach of infants and children
3) Do not store in hot or in daylight.
4. If the infant or child is mistakenly eaten, consult a medical doctor immediately and take emergency measures.
5. Over time, there may be sedimentation and slight discoloration due to the inclusion of natural ingredients, but threre is no abnormality inthe product.

KEEP OUT OF REACH OF CHILDREN

Please keep out of reach of infants and children

Uses

Helps brighten skin tone.
Helps improve wrinkle problem.

Directions

After cleansing or applying our ampoule, take an appropriate amount of this product and spread evenly on the skin.
*Over time, there may be sedimentation and slight discoloration due to the inclusion of natural ingredients, but there is no abnormality in the product.